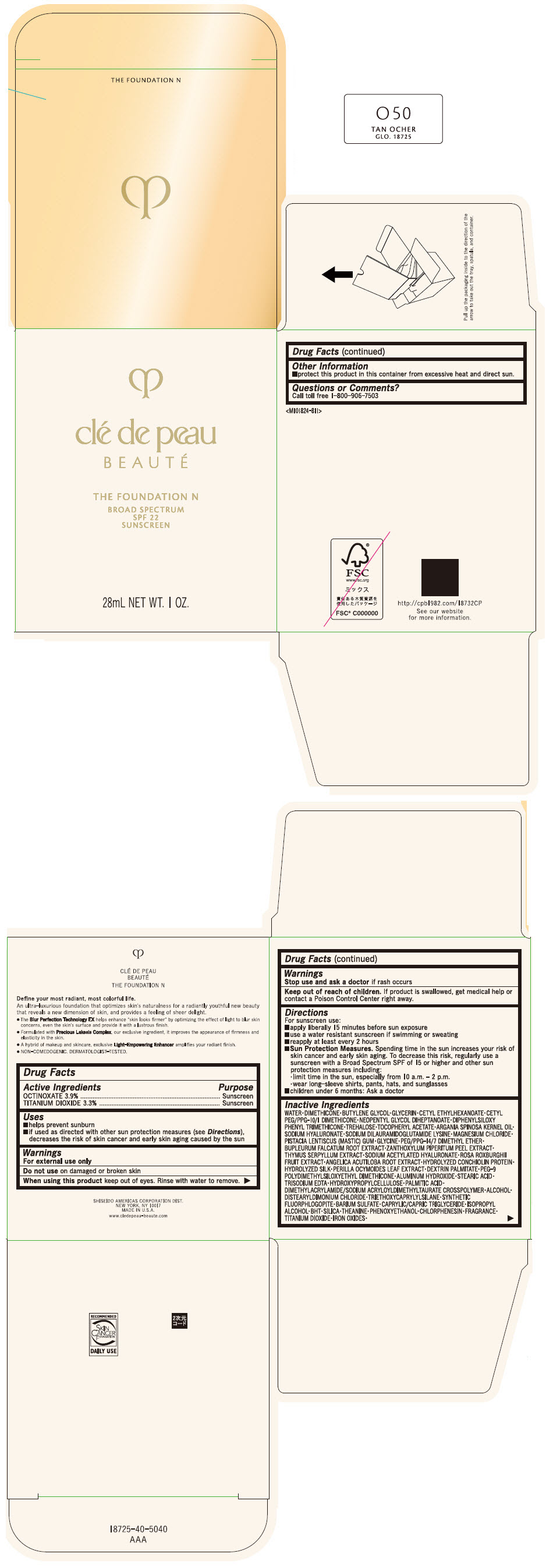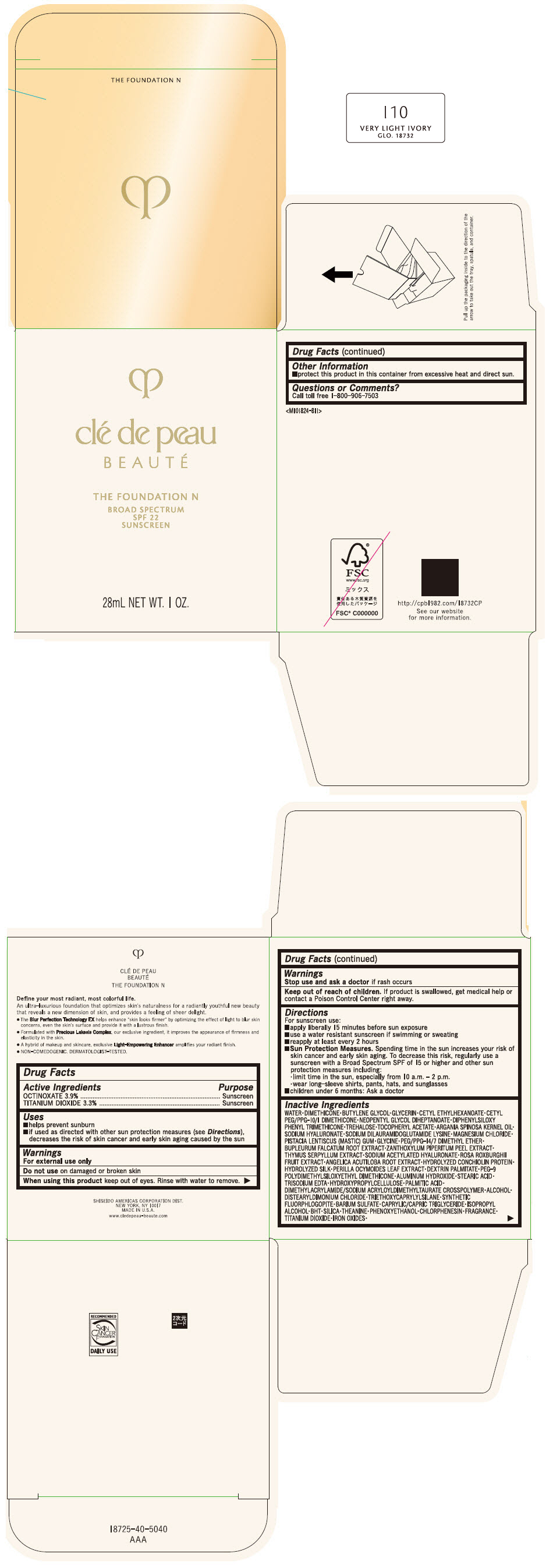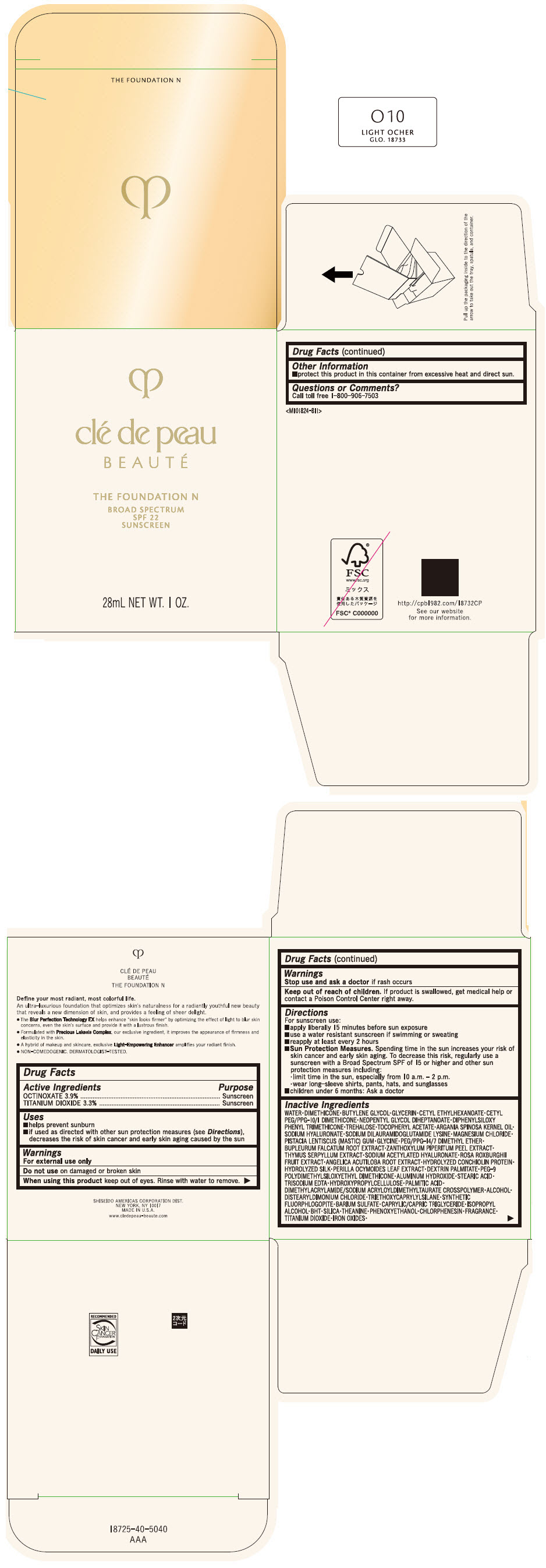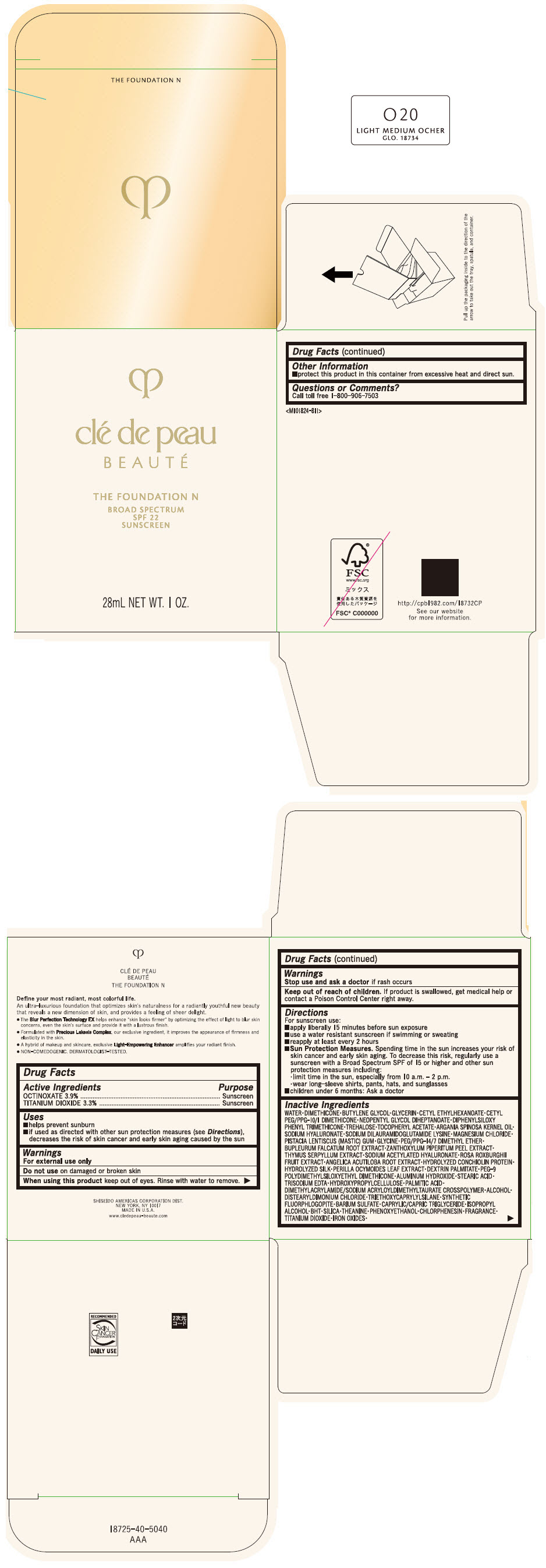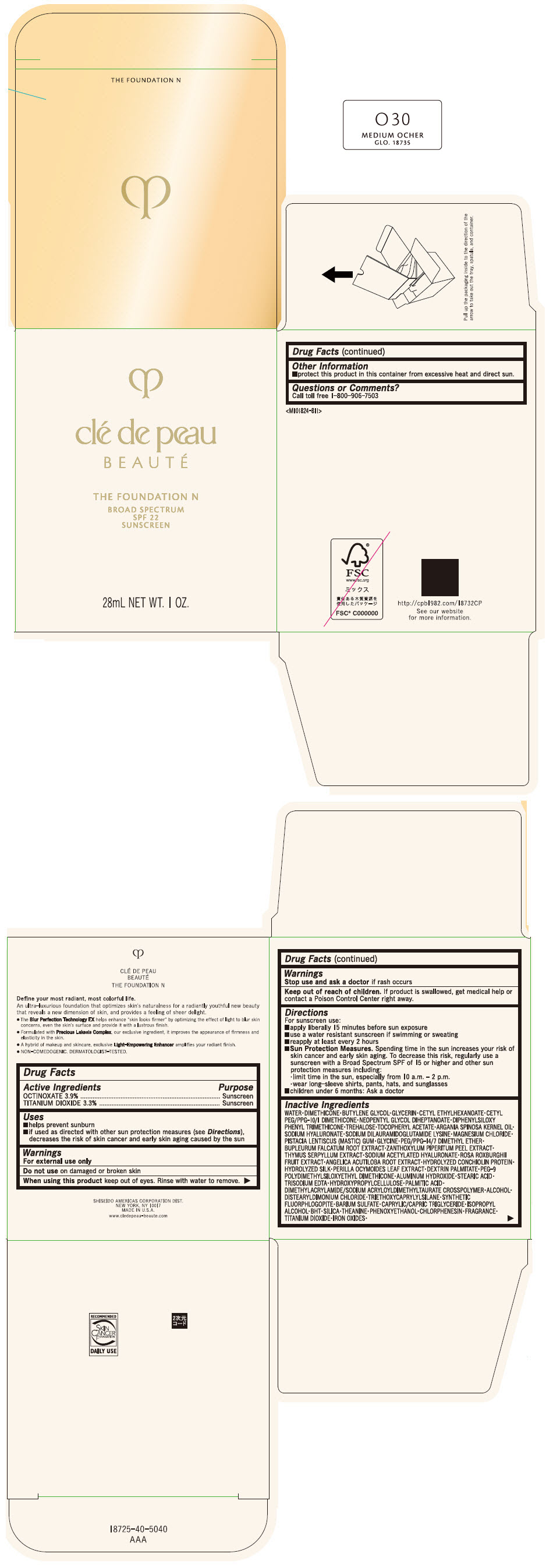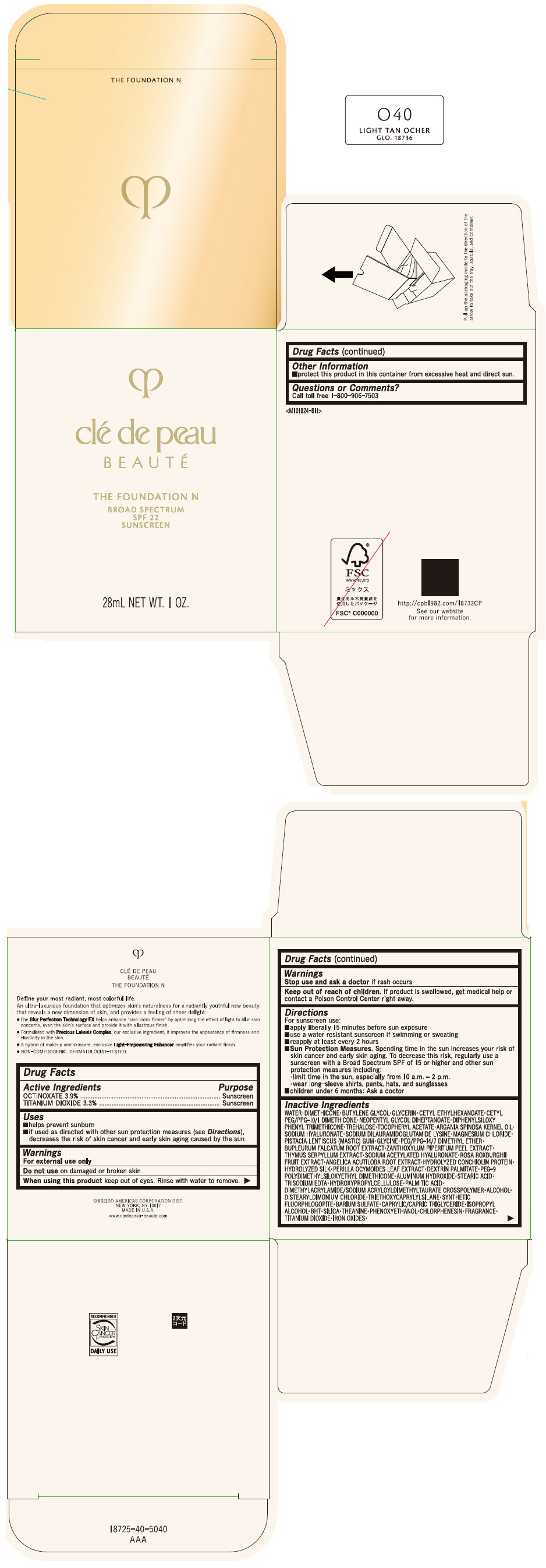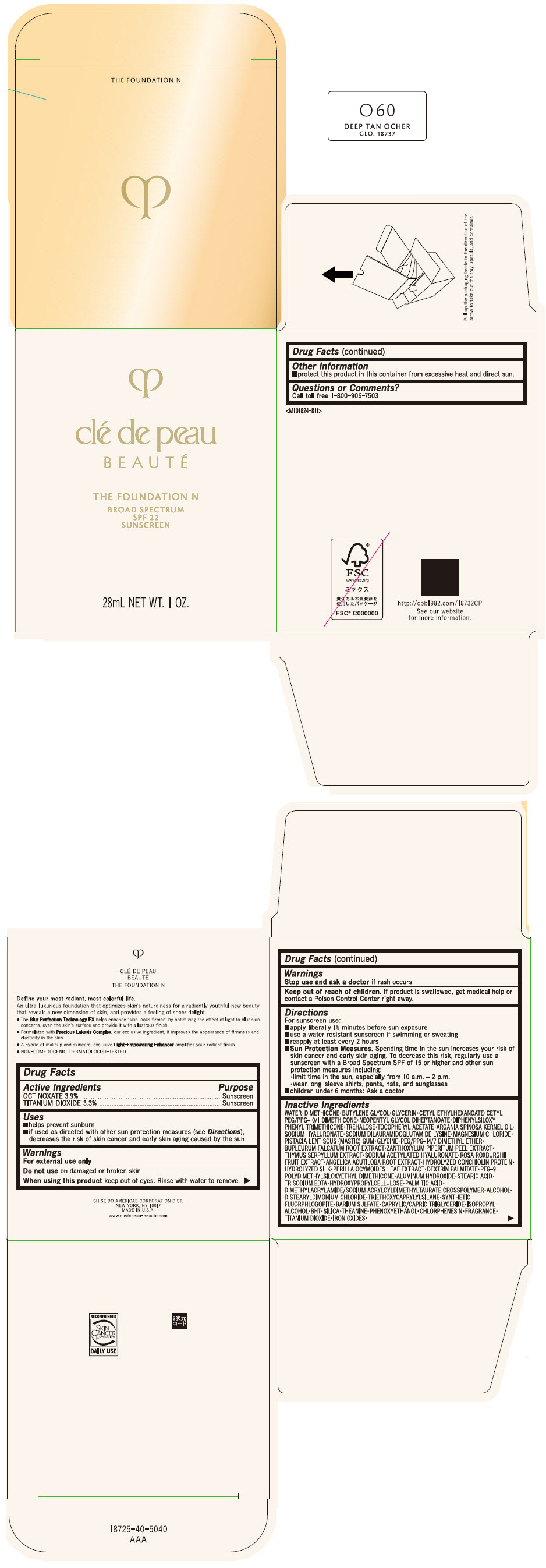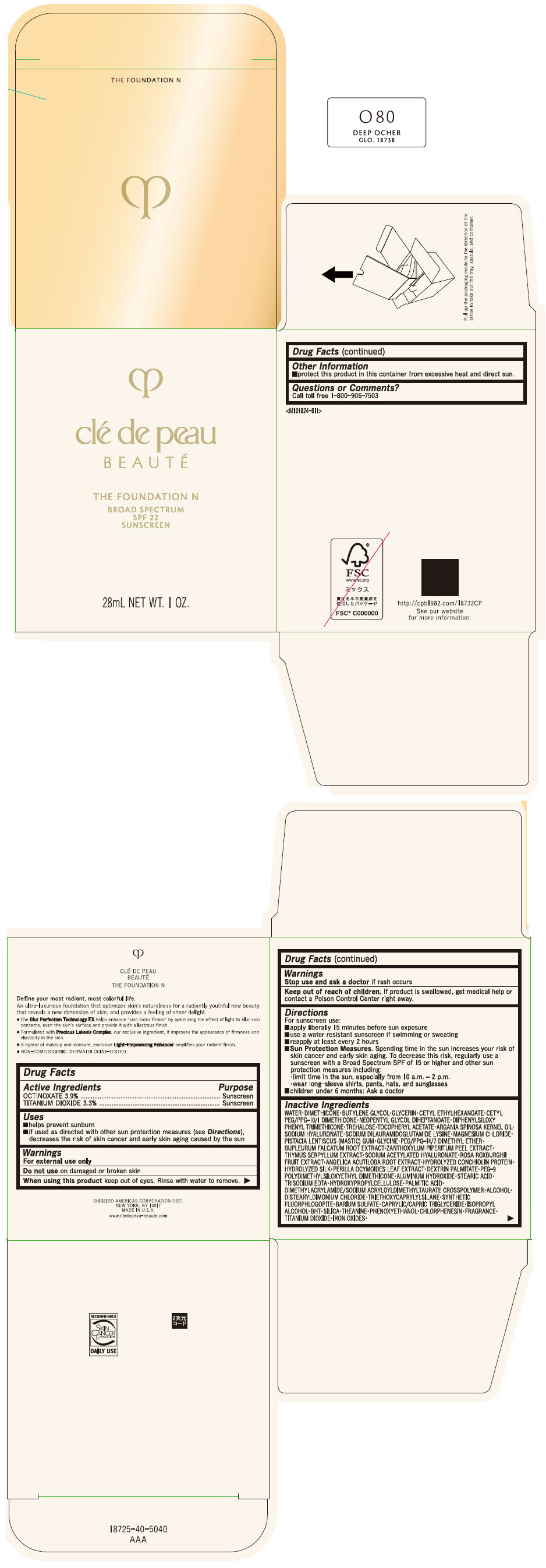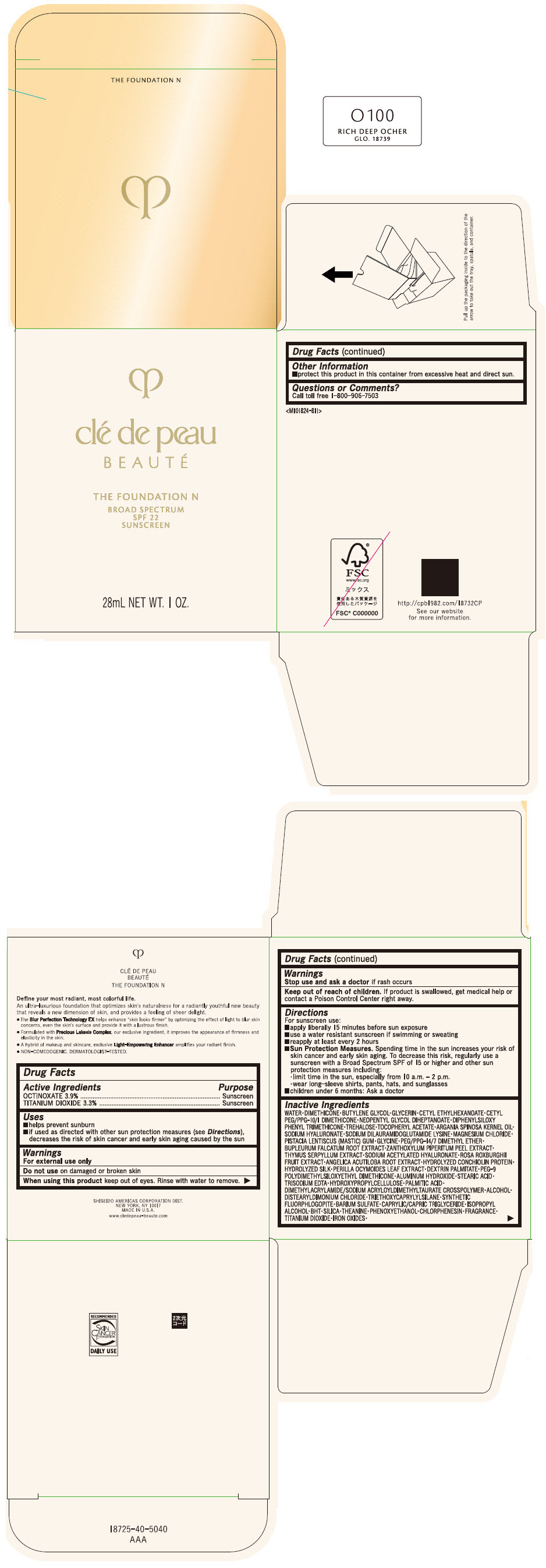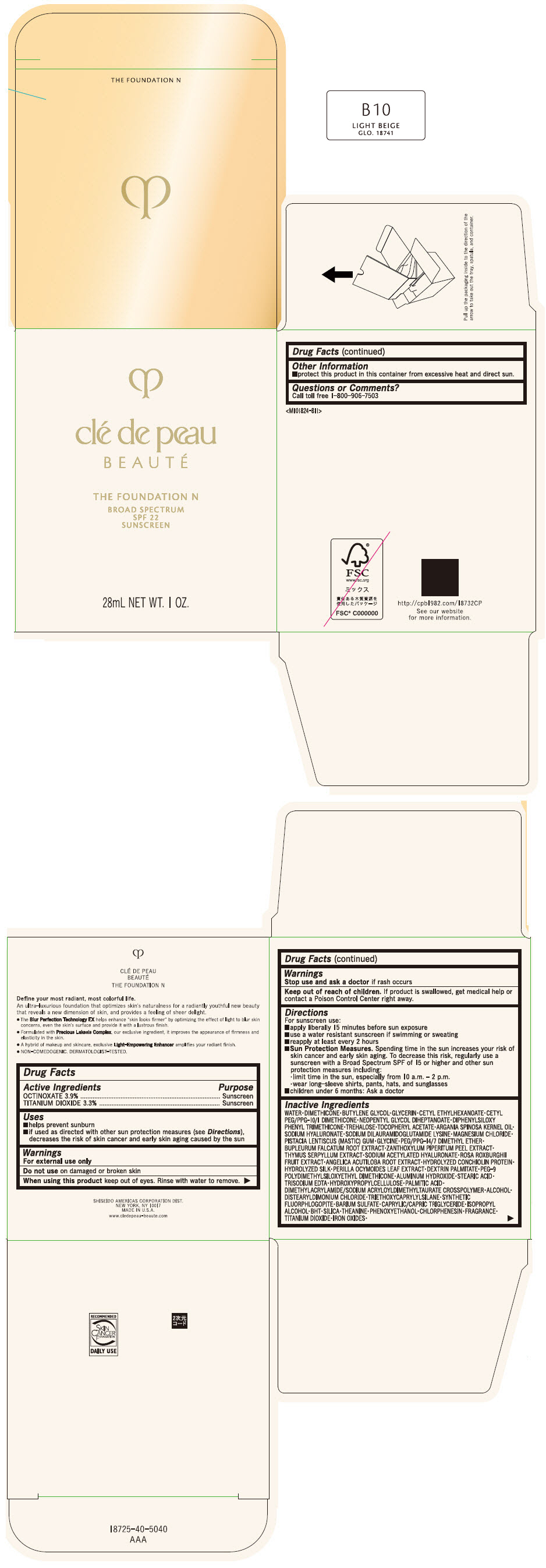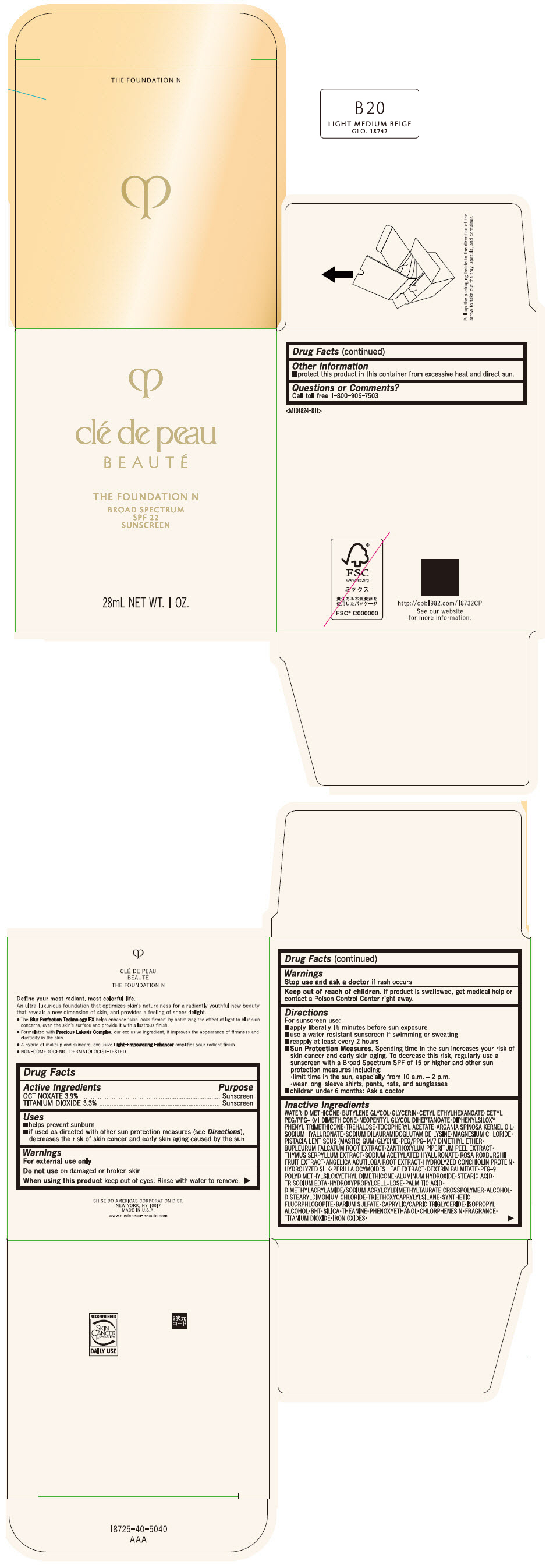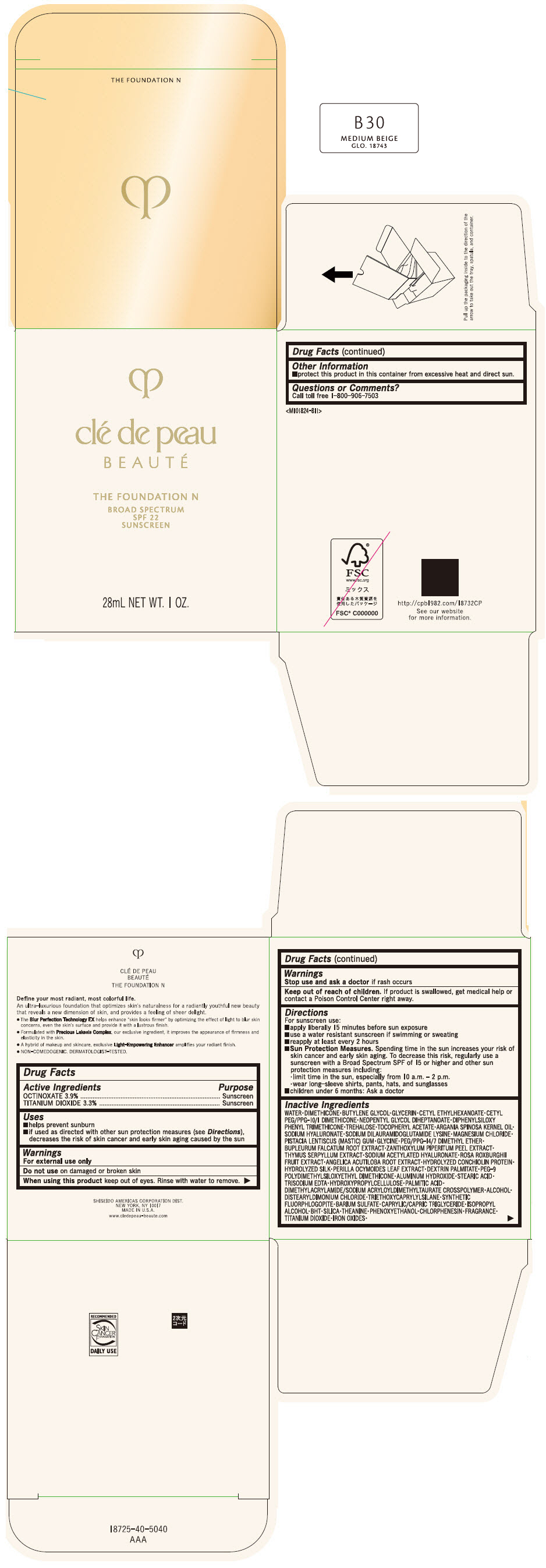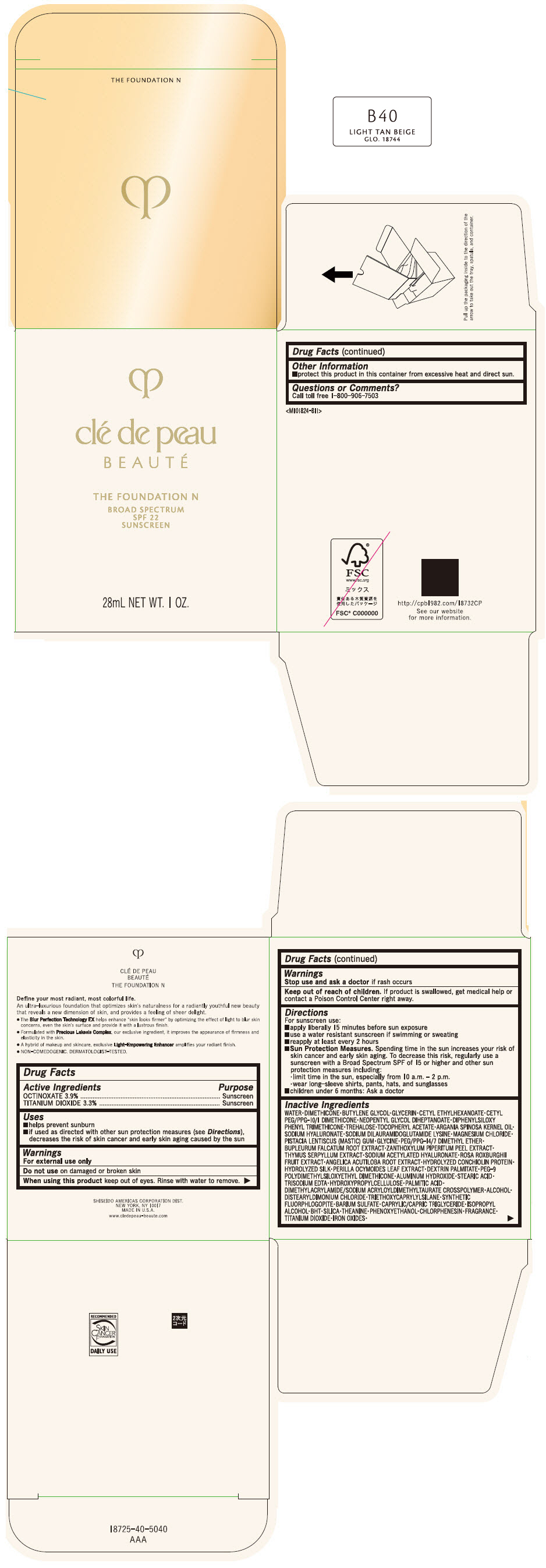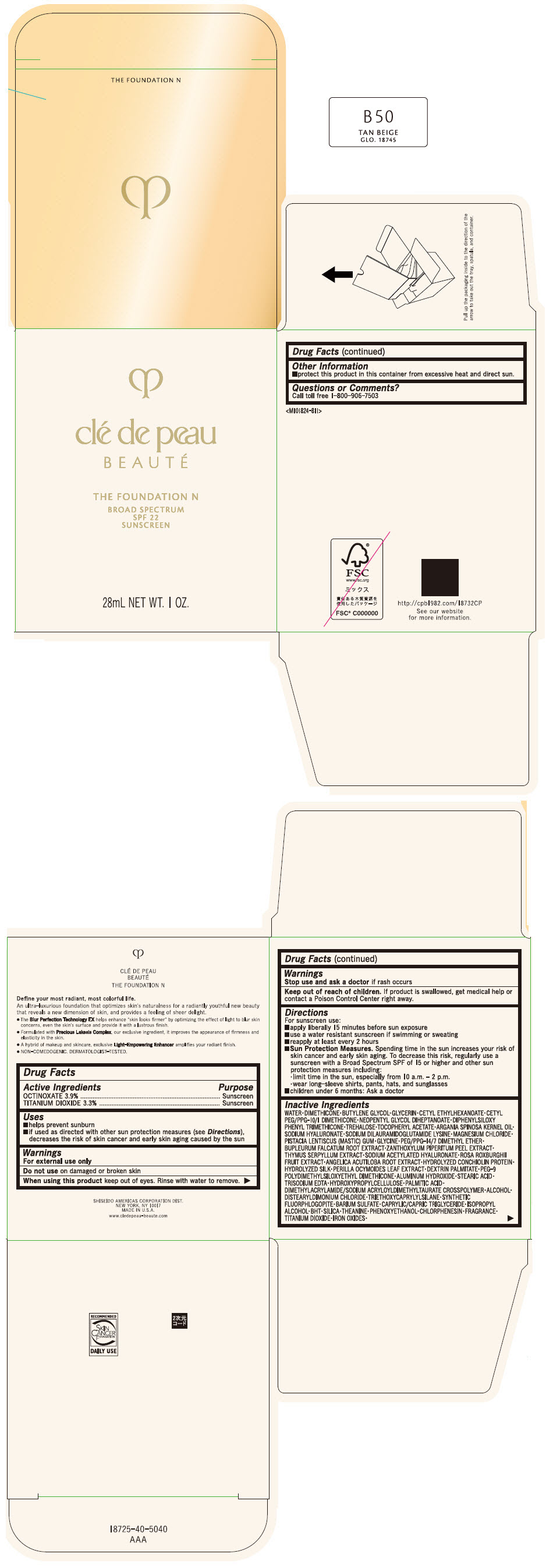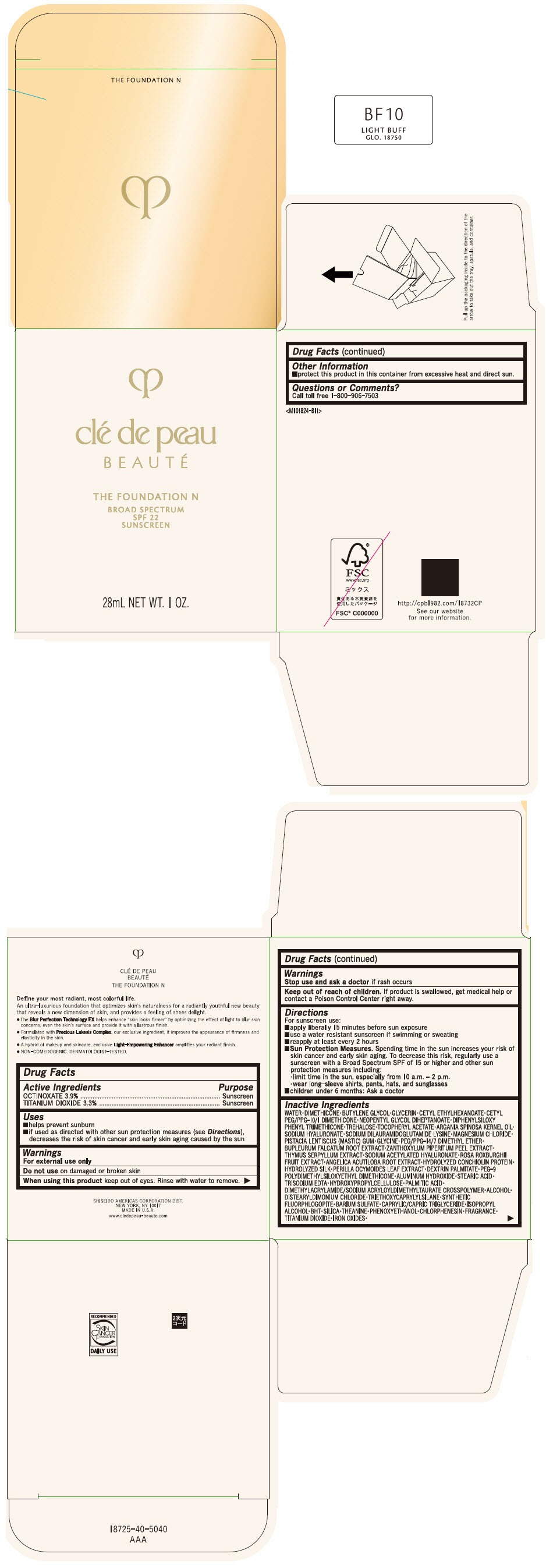 DRUG LABEL: cle de peau BEAUTE THE FOUNDATION N

NDC: 58411-839 | Form: EMULSION
Manufacturer: SHISEIDO AMERICAS CORPORATION
Category: otc | Type: HUMAN OTC DRUG LABEL
Date: 20260105

ACTIVE INGREDIENTS: OCTINOXATE 1092 mg/28 mL; TITANIUM DIOXIDE 924 mg/28 mL
INACTIVE INGREDIENTS: MAGNESIUM POTASSIUM ALUMINOSILICATE FLUORIDE; MEDIUM-CHAIN TRIGLYCERIDES; MAGNESIUM CHLORIDE; ISOPROPYL ALCOHOL; BUTYLATED HYDROXYTOLUENE; PISTACIA LENTISCUS RESIN; GLYCINE; PEG/PPG-14/7 DIMETHYL ETHER; SILICON DIOXIDE; THEANINE; BUPLEURUM FALCATUM ROOT; ZANTHOXYLUM PIPERITUM FRUIT RIND; THYMUS SERPYLLUM WHOLE; SODIUM ACETYLATED HYALURONATE; ROSA ROXBURGHII FRUIT; ANGELICA ACUTILOBA ROOT; WATER; DIMETHICONE; BUTYLENE GLYCOL; GLYCERIN; CETYL ETHYLHEXANOATE; NEOPENTYL GLYCOL DIHEPTANOATE; FERRIC OXIDE RED; DIPHENYLSILOXY PHENYL TRIMETHICONE; PHENOXYETHANOL; PEG-9 POLYDIMETHYLSILOXYETHYL DIMETHICONE; ALUMINUM HYDROXIDE; STEARIC ACID; CHLORPHENESIN; EDETATE TRISODIUM; ARGAN OIL; HYDROXYPROPYL CELLULOSE (1600000 WAMW); PALMITIC ACID; .ALPHA.-TOCOPHEROL ACETATE; TREHALOSE; ALCOHOL; HYALURONATE SODIUM; DISTEARYLDIMONIUM CHLORIDE; SODIUM DILAURAMIDOGLUTAMIDE LYSINE; TRIETHOXYCAPRYLYLSILANE; BARIUM SULFATE; PERILLA FRUTESCENS LEAF

clé de peau BEAUTÉ THE FOUNDATION N

Drug Facts

ACTIVE INGREDIENT

Active ingredients | Purpose
Octinoxate 3.9% | Sunscreen
Titanium Dioxide 3.3% | Sunscreen

Uses

- helps prevent sunburn
- if used as directed with other sun protection measures (see Directions), decreases the risk of skin cancer and early skin aging caused by the sun

Warnings

For external use only

Do not useon damaged or broken skin

WHEN USING

When using this productkeep out of eyes. Rinse with water to remove.

Stop use and ask a doctorif rash occurs.

Keep out of reach of children.If product is swallowed, get medical help or contact a Poison Control Center right away.

Directions

For sunscreen use:

- apply liberally 15 minutes before sun exposure
- use a water resistant sunscreen if swimming or sweating
- reapply at least every 2 hours
- Sun Protection Measures. Spending time in the sun increases your risk of skin cancer and early skin aging. To decrease this risk, regularly use a sunscreen with a Broad Spectrum SPF value of 15 or higher and other sun protection measures including:
  - limit time in the sun, especially from 10 a.m. – 2 p.m.
  - wear long-sleeve shirts, pants, hats, and sunglasses
- children under 6 months: Ask a doctor

Inactive Ingredients

WATER▪DIMETHICONE▪BUTYLENE GLYCOL▪GLYCERIN▪CETYL ETHYLHEXANOATE▪CETYL PEG/PPG-10/1 DIMETHICONE▪NEOPENTYL GLYCOL DIHEPTANOATE▪DIPHENYLSILOXY PHENYL TRIMETHICONE▪TREHALOSE▪TOCOPHERYL ACETATE▪ARGANIA SPINOSA KERNEL OIL▪SODIUM HYALURONATE▪SODIUM DILAURAMIDOGLUTAMIDE LYSINE▪MAGNESIUM CHLORIDE▪PISTACIA LENTISCUS (MASTIC) GUM▪GLYCINE▪PEG/PPG-14/7 DIMETHYL ETHER▪BUPLEURUM FALCATUM ROOT EXTRACT▪ZANTHOXYLUM PIPERITUM PEEL EXTRACT▪THYMUS SERPYLLUM EXTRACT▪SODIUM ACETYLATED HYALURONATE▪ROSA ROXBURGHII FRUIT EXTRACT▪ANGELICA ACUTILOBA ROOT EXTRACT▪HYDROLYZED CONCHIOLIN PROTEIN▪HYDROLYZED SILK▪PERILLA OCYMOIDES LEAF EXTRACT▪DEXTRIN PALMITATE▪PEG-9 POLYDIMETHYLSILOXYETHYL DIMETHICONE▪ALUMINUM HYDROXIDE▪STEARIC ACID▪TRISODIUM EDTA▪HYDROXYPROPYLCELLULOSE▪PALMITIC ACID▪DIMETHYLACRYLAMIDE/SODIUM ACRYLOYLDIMETHYLTAURATE CROSSPOLYMER▪ALCOHOL▪DISTEARYLDIMONIUM CHLORIDE▪TRIETHOXYCAPRYLYLSILANE▪SYNTHETIC FLUORPHLOGOPITE▪BARIUM SULFATE▪CAPRYLIC/CAPRIC TRIGLYCERIDE▪ISOPROPYL ALCOHOL▪BHT▪SILICA▪THEANINE▪PHENOXYETHANOL▪CHLOROPHENESIN▪FRAGRANCE▪TITANIUM DIOXIDE▪IRON OXIDES▪

Other information

- protect this product in this container from excessive heat and direct sun.

Questions or Comments?

Call toll free 1-800-906-7503

PRINCIPAL DISPLAY PANEL - 28 mL Bottle Box - O50 Tan Ocher

clé de peau

B E A U T É

THE FOUNDATION N

BROAD SPECTRUM
SPF 22
SUNSCREEN

28mL NET WT. 1 OZ.

PRINCIPAL DISPLAY PANEL - 28 mL Bottle Box - I10 Very Light Ivory

clé de peau

B E A U T É

THE FOUNDATION N

BROAD SPECTRUM
SPF 22
SUNSCREEN

28mL NET WT. 1 OZ.

PRINCIPAL DISPLAY PANEL - 28 mL Bottle Box - O10 Light Ocher

clé de peau

B E A U T É

THE FOUNDATION N

BROAD SPECTRUM
SPF 22
SUNSCREEN

28mL NET WT. 1 OZ.

PRINCIPAL DISPLAY PANEL - 28 mL Bottle Box - O20 Light Medium Ocher

clé de peau

B E A U T É

THE FOUNDATION N

BROAD SPECTRUM
SPF 22
SUNSCREEN

28mL NET WT. 1 OZ.

PRINCIPAL DISPLAY PANEL - 28 mL Bottle Box - O30 Medium Ocher

clé de peau

B E A U T É

THE FOUNDATION N

BROAD SPECTRUM
SPF 22
SUNSCREEN

28mL NET WT. 1 OZ.

PRINCIPAL DISPLAY PANEL - 28 mL Bottle Box - O40 Light Tan Ocher

clé de peau

B E A U T É

THE FOUNDATION N

BROAD SPECTRUM
SPF 22
SUNSCREEN

28mL NET WT. 1 OZ.

PRINCIPAL DISPLAY PANEL - 28 mL Bottle Box - O60 Deep Tan Ocher

clé de peau

B E A U T É

THE FOUNDATION N

BROAD SPECTRUM
SPF 22
SUNSCREEN

28mL NET WT. 1 OZ.

PRINCIPAL DISPLAY PANEL - 28 mL Bottle Box - O80 Deep Ocher

clé de peau

B E A U T É

THE FOUNDATION N

BROAD SPECTRUM
SPF 22
SUNSCREEN

28mL NET WT. 1 OZ.

PRINCIPAL DISPLAY PANEL - 28 mL Bottle Box - O100 Rich Deep Ocher

clé de peau

B E A U T É

THE FOUNDATION N

BROAD SPECTRUM
SPF 22
SUNSCREEN

28mL NET WT. 1 OZ.

PRINCIPAL DISPLAY PANEL - 28 mL Bottle Box - B10 Light Beige

clé de peau

B E A U T É

THE FOUNDATION N

BROAD SPECTRUM
SPF 22
SUNSCREEN

28mL NET WT. 1 OZ.

PRINCIPAL DISPLAY PANEL - 28 mL Bottle Box - B20 Light Medium Beige

clé de peau

B E A U T É

THE FOUNDATION N

BROAD SPECTRUM
SPF 22
SUNSCREEN

28mL NET WT. 1 OZ.

PRINCIPAL DISPLAY PANEL - 28 mL Bottle Box - B30 Medium Beige

clé de peau

B E A U T É

THE FOUNDATION N

BROAD SPECTRUM
SPF 22
SUNSCREEN

28mL NET WT. 1 OZ.

PRINCIPAL DISPLAY PANEL - 28 mL Bottle Box - B40 Light Tan Beige

clé de peau

B E A U T É

THE FOUNDATION N

BROAD SPECTRUM
SPF 22
SUNSCREEN

28mL NET WT. 1 OZ.

PRINCIPAL DISPLAY PANEL - 28 mL Bottle Box - B50 Tan Beige

clé de peau

B E A U T É

THE FOUNDATION N

BROAD SPECTRUM
SPF 22
SUNSCREEN

28mL NET WT. 1 OZ.

PRINCIPAL DISPLAY PANEL - 28 mL Bottle Box - BF10 Light Buff

clé de peau

B E A U T É

THE FOUNDATION N

BROAD SPECTRUM
SPF 22
SUNSCREEN

28mL NET WT. 1 OZ.